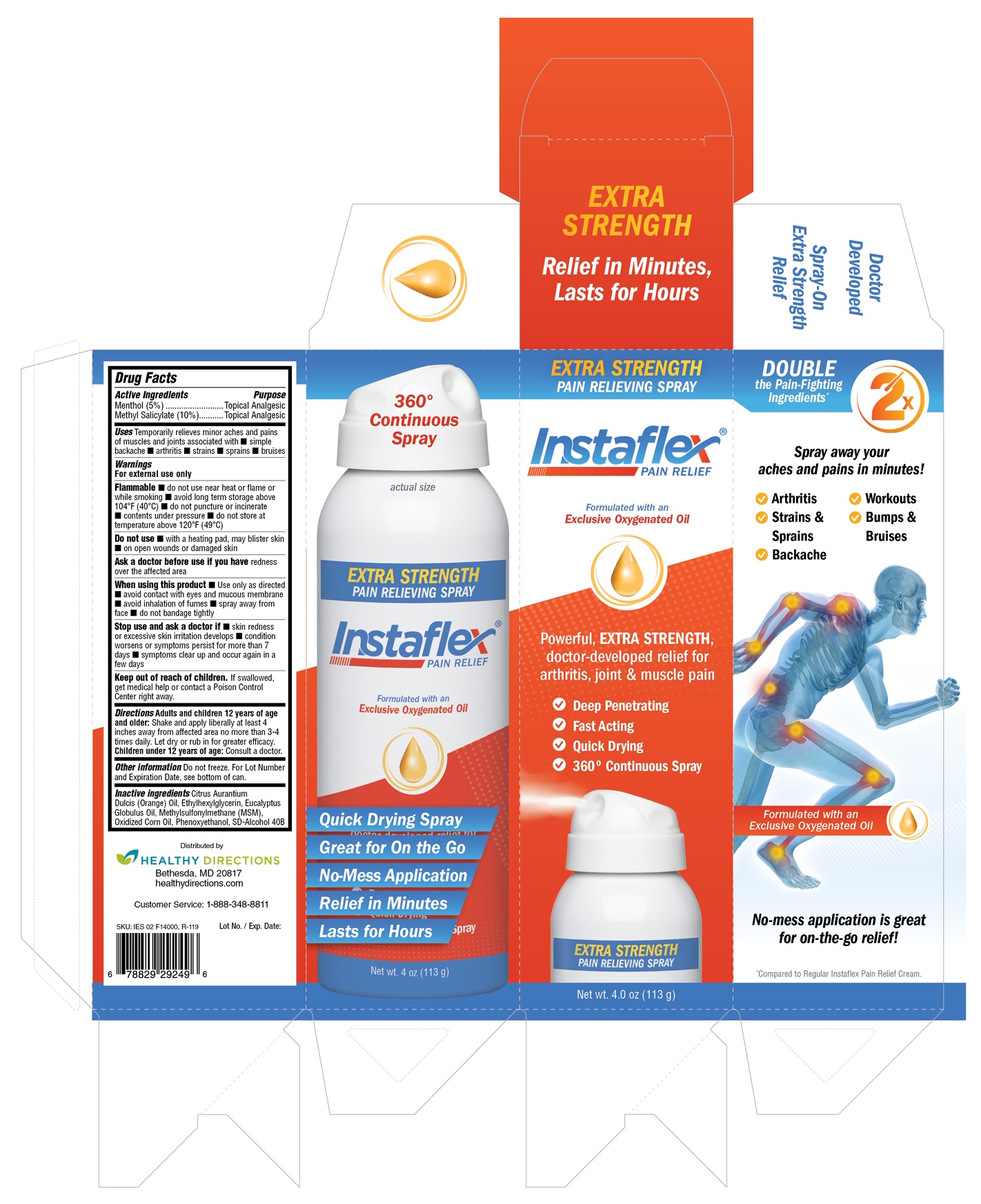 DRUG LABEL: Instaflex Pain Relief
NDC: 70015-675 | Form: SPRAY
Manufacturer: Healthy Directions, LLC
Category: otc | Type: HUMAN OTC DRUG LABEL
Date: 20191211

ACTIVE INGREDIENTS: MENTHOL 50 mg/1 g; METHYL SALICYLATE 100 mg/1 g
INACTIVE INGREDIENTS: CORN OIL; PHENOXYETHANOL; ETHYLHEXYLGLYCERIN; ORANGE OIL; EUCALYPTUS OIL; DIMETHYL SULFONE; ALCOHOL

InstaFlex Pain Relieving Spray

Active Ingredients

Menthol (5%)

Methyl Salicylate (10%)

Purpose

Menthol (5%)....................Topical Analgesic

Methyl Salicylate (10%)....................Topical Analgesic

Uses

Temporarily relieves minor aches and pains of muscles and joints associated with

- simple backache
- arthritis
- strains
- sprains
- bruises

Warnings

For external use only

Flammable

- do not use near heat or flame or while smoking
- avoid long term storage above 104F (40C)
- do not puncture or incinerate
- contents under pressure
- do not store at temperature above 120F (49C)

Do not use

- with a heating pad, may blister skin
- on open wounds or damaged skin

Ask a doctor before use if you have redness over the affected area

When using this product

- Use only as directed
- avoid contact with eyes and mucous membrane
- avoid inhalation of fumes
- spray away from face
- do not bandage tightly

Stop use and ask a doctor if

- skin redness or excessive skin irritation develops
- condition worsens or symptoms persist for more than 7 days
- symptoms clear up and occur again in a few days

Keep out of reach of children. If swallowed, get medical help or contact a Poison Control Center right away.

Directions

Adult and children 12 years of age and older: Shake and apply liberally at least 4 inches away from affected area no more than 3-4 times daily. Let dry or rub in for greater efficacy.

Children under 12 years of age: Consult a doctor.

Other information

Do not freeze. For Lot Number and Expiration Date, see bottom of can.

Inactive ingredients

Citrus Aurantium Dulcis (Orange) Oil, Ethylhexylglycerin, Eucalyptus Globulus Oil, Methylsulfonylmethane (MSM), Oxidized Corn Oil, Phenoxyethanol, SD-Alcohol 40B.

PACKAGE LABEL

EXTRA STRENGTH

PAIN RELIEVING SPRAY

Instaflex

PAIN RELIEF

Formualted with an Exclusive Oxygenated Oil

Powerful, EXTRA STRENGTH, doctor-developed relief for arthritis, joint & muscle pain

- Deep Penetrating
- Fast Acting
- Quick Drying
- 360 Continuous Spray

EXTRA STRENGTH

PAIN RELIEVING SPRAY

Net wt. 4.0 oz (113 g)